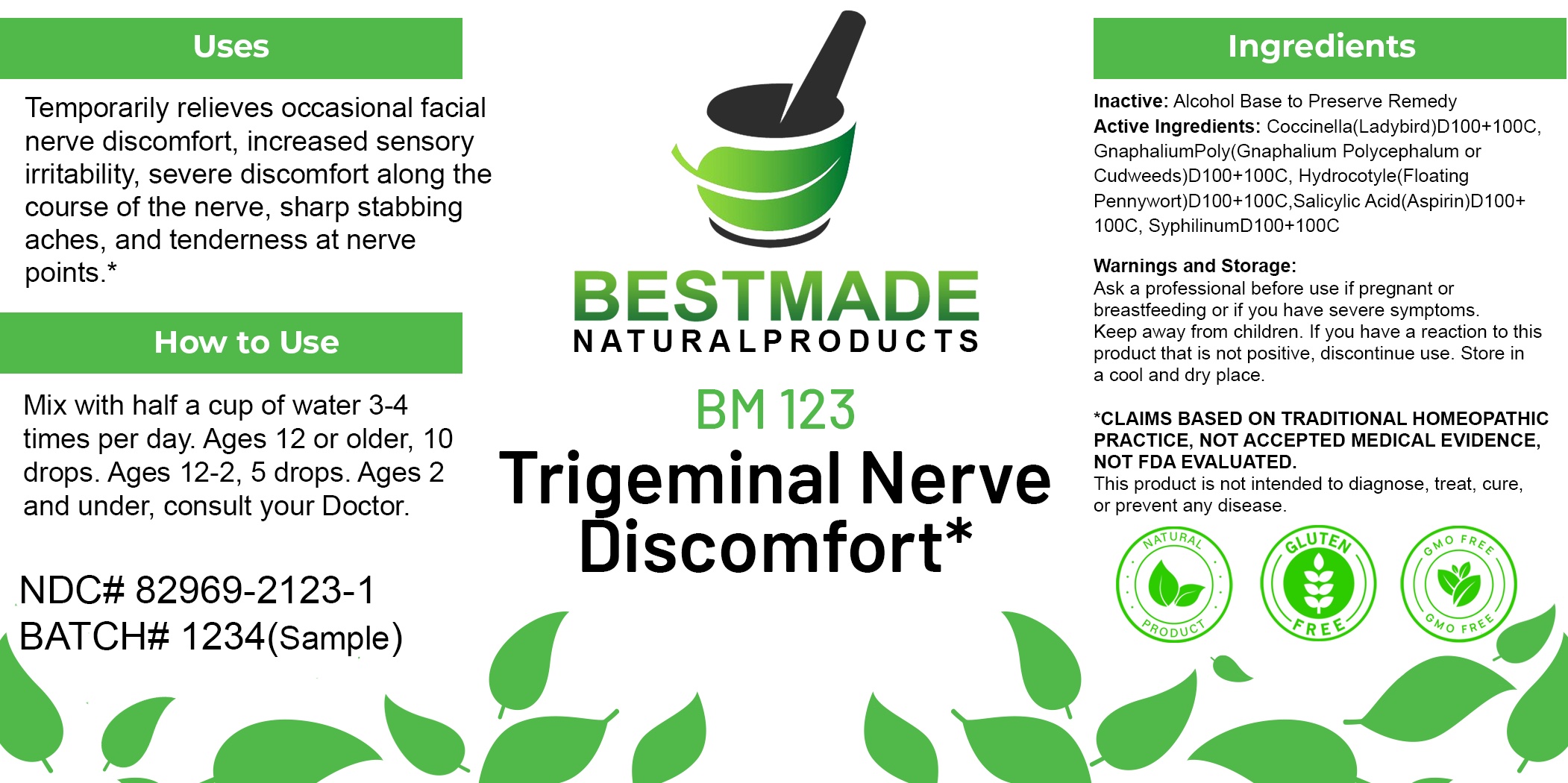 DRUG LABEL: Bestmade Natural Products BM123
NDC: 82969-2123 | Form: LIQUID
Manufacturer: Bestmade Natural Products
Category: homeopathic | Type: HUMAN OTC DRUG LABEL
Date: 20250207

ACTIVE INGREDIENTS: COCCINELLA SEPTEMPUNCTATA 30 [hp_C]/30 [hp_C]; SALICYLIC ACID 30 [hp_C]/30 [hp_C]; PSEUDOGNAPHALIUM OBTUSIFOLIUM 30 [hp_C]/30 [hp_C]; TREPONEMIC SKIN CANKER HUMAN 30 [hp_C]/30 [hp_C]; CENTELLA ASIATICA 30 [hp_C]/30 [hp_C]
INACTIVE INGREDIENTS: ALCOHOL 30 [hp_C]/30 [hp_C]

BM123

DOSAGE AND ADMINISTRATION

How to Use

Mix with half a cup of water 3-4 times per day. Ages 12 or older, 10 drops. Ages 12-2, 5 drops. Ages 2 and under, consult your Doctor.

Inactive:

Alcohol Base to Preserve Product

ACTIVE INGREDIENTS

CoccinellaD100 100C, Gnaphalium PolyD100 100C, HydrocotyleD100 100C, Salicylic AcidD100 100C, SyphilinumD100 100C

Uses
Temporarily relieves occasional facial nerve discomfort, increased sensory irritability, severe discomfort along the course of the nerve, sharp stabbing aches, and tenderness at nerve points.*

Uses
Temporarily relieves occasional facial nerve discomfort, increased sensory irritability, severe discomfort along the course of the nerve, sharp stabbing aches, and tenderness at nerve points.*

KEEP OUT OF REACH OF CHILDREN

Warnings and Storage:

Ask a professional before use if pregnant or breastfeeding or if you have severe symptoms.

Keep away from children. If you have a reaction to this product that is not positive, discontinue use. Store in a cool and dry place

*CLAIMS BASED ON TRADITIONAL HOMEOPATHIC PRACTICE, NOT ACCEPTED MEDICAL EVIDENCE NOT FDA EVALUATED.
This product is not intended to diagnose, treat, cure, or prevent any disease.

Warnings and Storage:

Ask a professional before use if pregnant or breastfeeding or if you have severe symptoms.

Keep away from children. If you have a reaction to this product that is not positive, discontinue use. Store in a cool and dry place

*CLAIMS BASED ON TRADITIONAL HOMEOPATHIC PRACTICE, NOT ACCEPTED MEDICAL EVIDENCE NOT FDA EVALUATED.
This product is not intended to diagnose, treat, cure, or prevent any disease.

Entire package label